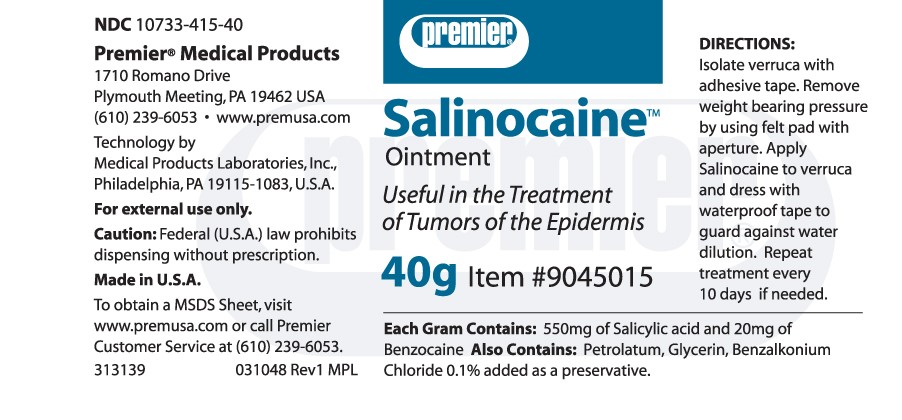 DRUG LABEL: Salinocaine
NDC: 10733-415 | Form: OINTMENT
Manufacturer: Medical Products Laboratories, Inc.
Category: prescription | Type: HUMAN PRESCRIPTION DRUG LABEL
Date: 20240807

ACTIVE INGREDIENTS: SALICYLIC ACID 550 mg/1 g; BENZOCAINE 20 mg/1 g
INACTIVE INGREDIENTS: PETROLATUM; GLYCERIN; BENZALKONIUM CHLORIDE

SALINOCAINE OINTMENT

DIRECTIONS Isolate verruca with adhesive tape. Remove weight bearing pressure by using felt pad with aperture. Apply Salinocaine to verruca and dress with waterproof tape to guard against water dilution. Repeat treatment every 10 days if needed.

Each Gram Contains: 550mg of Salicylic acid and 20mg of Benzocaine. Also Contains: Petrolatum, Glycerin, Benzalkonium Chloride 0.1% added as a preservative.

Premier® Medical Products 1710 Romano Drive Plymouth Meeting, PA 19462 USA (610) 239-6053 www.premusa.com

Technology by Medical Products Laboratories, Inc. Philadelphia, PA 19115-1083, U.S.A.

For external use only.
Caution: Federal (U.S.A.) law prohibits dispensing without prescription.
Made in U.S.A.

To obtain a MSDS Sheet, visit www.premusa.com or call Premier Customer Service at (610) 239-6053.